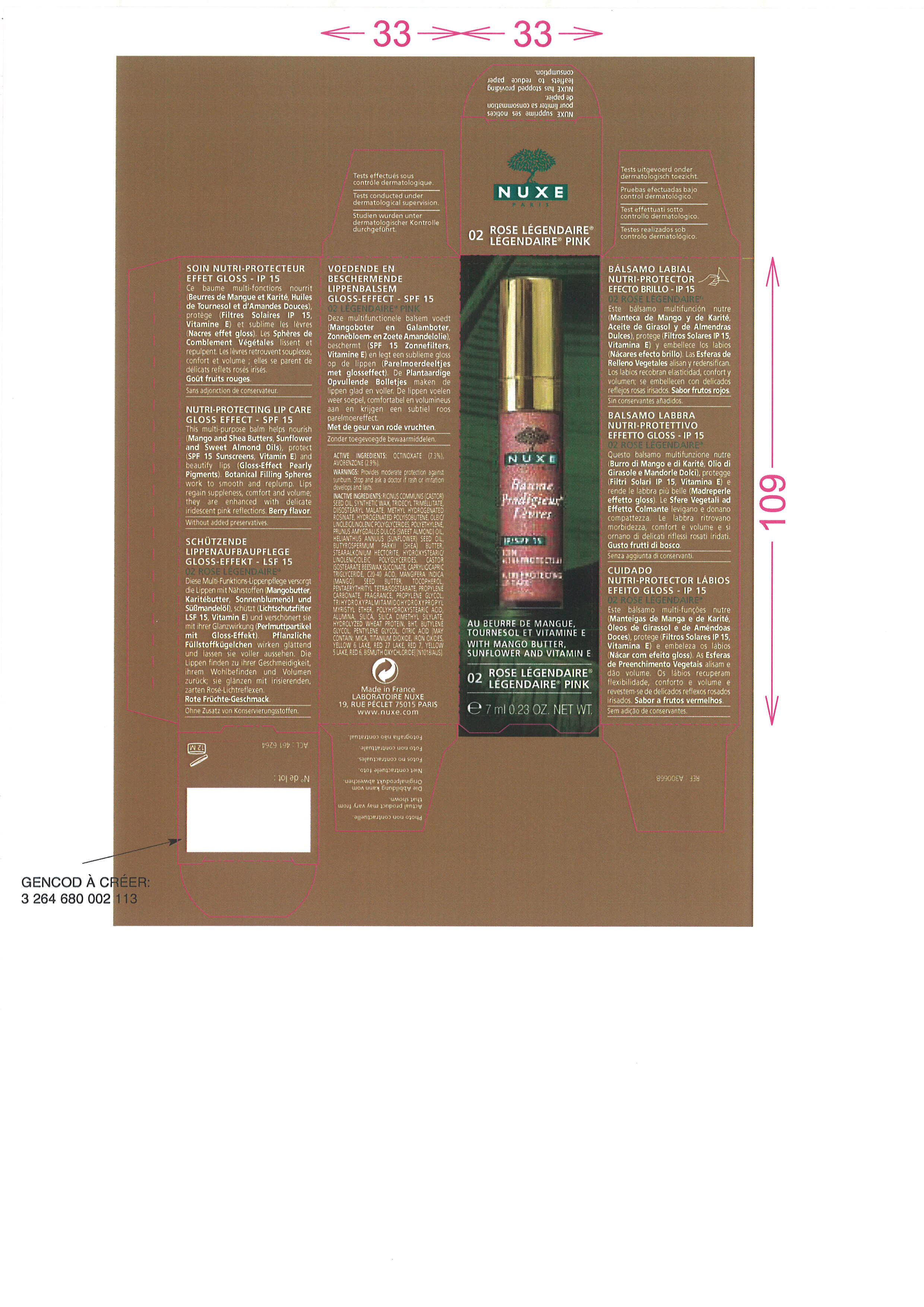 DRUG LABEL: BAUME PRODIGIEUX LEVRES 02 LEGENDAIRE PINK
NDC: 67542-020 | Form: LIPSTICK
Manufacturer: LABORATOIRE NUXE
Category: otc | Type: HUMAN OTC DRUG LABEL
Date: 20091201

ACTIVE INGREDIENTS: OCTINOXATE 7.3 mL/100 mL; AVOBENZONE 2.9 mL/100 mL
INACTIVE INGREDIENTS: CASTOR OIL; SYNTHETIC WAX (1200 MW); TRIDECYL TRIMELLITATE; DIISOSTEARYL MALATE; HYDROGENATED POLYBUTENE (1300 MW); HIGH DENSITY POLYETHYLENE; MICA; ALMOND OIL; SUNFLOWER OIL; SHEA BUTTER; TITANIUM DIOXIDE; MEDIUM-CHAIN TRIGLYCERIDES; C20-40 ACID; MANGIFERA INDICA SEED BUTTER; TOCOPHEROL; PENTAERYTHRITYL TETRAISOSTEARATE; PROPYLENE CARBONATE; TRIHYDROXYPALMITAMIDOHYDROXYPROPYL MYRISTYL ETHER; FERRIC OXIDE RED; POLYHYDROXYSTEARIC ACID (2300 MW); ALUMINUM OXIDE; SILICON DIOXIDE; SILICA DIMETHYL SILYLATE; HYDROLYZED WHEAT PROTEIN (ENZYMATIC, 3000 MW); BUTYLATED HYDROXYTOLUENE; BUTYLENE GLYCOL; PENTYLENE GLYCOL; CITRIC ACID MONOHYDRATE

Drug Facts

ACTIVE INGREDIENT

OCTINOXATE (7.3%), AVOBENZONE (2.9%)

PURPOSE

Provides moderate protection against sunburn.

PACKAGE LABEL

ACTIVE INGREDIENTS : OCTINOXATE (7.3%), AVOBENZONE (2.9%)
WARNINGS : Provides moderate protection against sunburn. Stop and ask a doctor if rash or irritation develops and lasts.